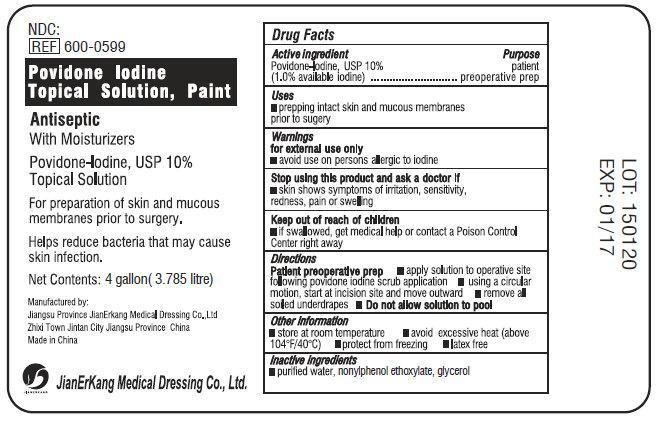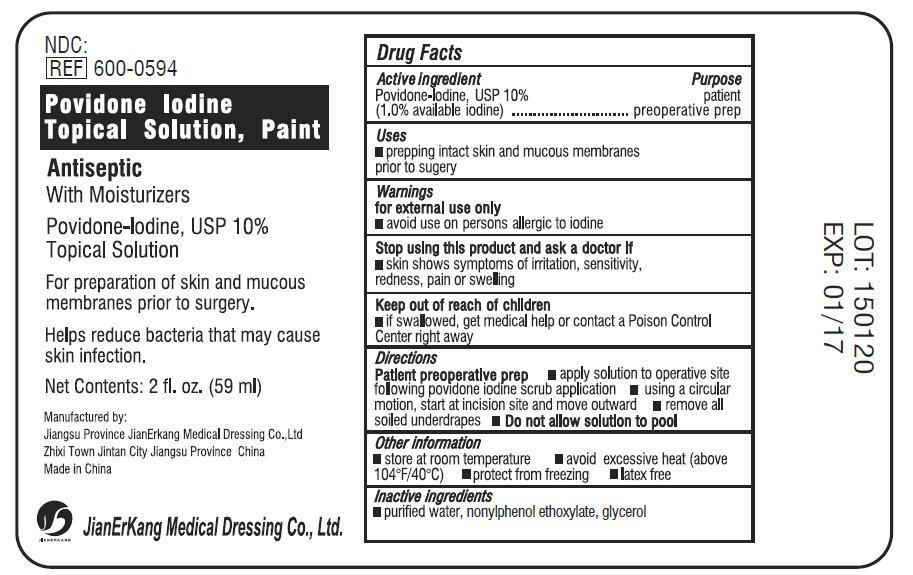 DRUG LABEL: Povidone Iodine Topical Solution Paint
NDC: 34645-1040 | Form: LIQUID
Manufacturer: Jianerkang Medical Co., Ltd
Category: otc | Type: HUMAN OTC DRUG LABEL
Date: 20231022

ACTIVE INGREDIENTS: POVIDONE-IODINE 100 mg/1 mL
INACTIVE INGREDIENTS: WATER; NONOXYNOL-9; GLYCERIN

Povidone Iodine Topical Solution Paint

Drug Facts

Active Ingredient

Povidone-Iodine, USP 10%

(1.0% available iodine)

Purpose

patient preoperative prep

Use

prepping intact skin and mucous membranes prior to sugery

Warnings

for external use only

avoid use on persons allergic to iodine

Stop using this product and ask a doctor if

- skin shows symptoms of irritation, sensitivity, redness, pain or swelling

Keep out of reach of children.

if swallowed, get medical help or contact a Poison Control Center right away

Directions

Patient preoperative prep

- apply solution to operative site following povidone iodine scrub application
- using a circular motion, start at incision site and move outward
- remove all soiled underdrapes
- do no allow solution to pool

Other information

- store at room temperature
- avoid excessive heat (above 104 degrees F/40 degrees C)
- protect from freezing
- latex free

Inactive Ingredients

Purified Water, nonylphenol ethoxylate, glycerol